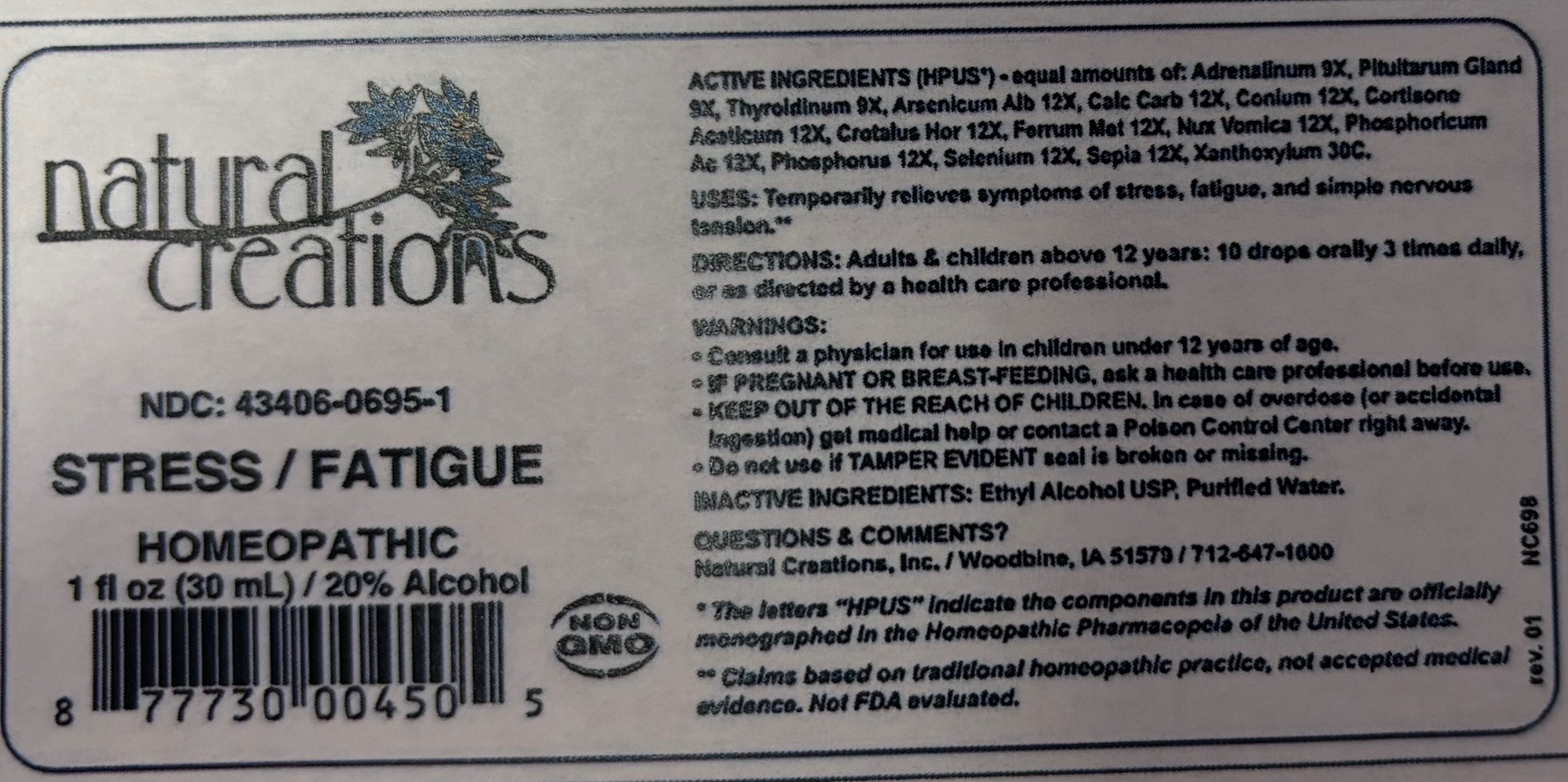 DRUG LABEL: STRESS / FATIGUE
NDC: 43406-0695 | Form: LIQUID
Manufacturer: Natural Creations, Inc.
Category: homeopathic | Type: HUMAN OTC DRUG LABEL
Date: 20250702

ACTIVE INGREDIENTS: EPINEPHRINE 9 [hp_X]/1 mL; SUS SCROFA PITUITARY GLAND, POSTERIOR 9 [hp_X]/1 mL; THYROID 9 [hp_X]/1 mL; ARSENIC TRIOXIDE 12 [hp_X]/1 mL; OYSTER SHELL CALCIUM CARBONATE, CRUDE 12 [hp_X]/1 mL; CONIUM MACULATUM FLOWERING TOP 12 [hp_X]/1 mL; CORTISONE ACETATE 12 [hp_X]/1 mL; CROTALUS HORRIDUS HORRIDUS VENOM 12 [hp_X]/1 mL; IRON 12 [hp_X]/1 mL; STRYCHNOS NUX-VOMICA SEED 12 [hp_X]/1 mL; PHOSPHORIC ACID 12 [hp_X]/1 mL; PHOSPHORUS 12 [hp_X]/1 mL; SELENIUM 12 [hp_X]/1 mL; SEPIA OFFICINALIS JUICE 12 [hp_X]/1 mL; ZANTHOXYLUM AMERICANUM BARK 30 [hp_C]/1 mL
INACTIVE INGREDIENTS: ALCOHOL; WATER

STRESS / FATIGUE

ACTIVE INGREDIENT

ACTIVE INGREDIENTS (HPUS*) - equal amounts of: Adrenalinum 9X, Pituitary Gland 9X, Thyroidinum 9X, Arsenicum Alb 12X, Calc Carb 12X, Conium 12X, Cortisone Aceticum 12X, Crotalus Hor 12X, Ferrum Met 12X, Nux Vomica 12X, Phosphoricum Ac 12X, Phosphorus 12X, Selenium 12X Sepia 12X, Xanthoxylum 30C.

PURPOSE

USES: Temporarily relieves symptoms of stress, fatigue, and simple nervous tension.**

INDICATIONS AND USAGE

USES: Temporarily relieves symptoms of stress, fatigue, and simple nervous tension.**

DOSAGE AND ADMINISTRATION

DIRECTIONS: Adults and children above 12 years: 10 drops orally 3 times daily, or as directed by a health care professional.

WARNINGS:

- Consult a physician for use in children under 12 years of age.
- IF PREGNANT OR BREAST-FEEDING, ask a health care professional before use.
- KEEP OUT OF THE REACH OF CHILDREN. In case of overdose (or accidental ingestion) get medical help or contact Poison Control Center right away.
- Do not use if TAMPER EVIDENT seal is broken or missing.

WARNINGS:

- Consult a physician for use in children under 12 years of age.
- IF PREGNANT OR BREAST-FEEDING, ask a health care professional before use.
- KEEP OUT OF THE REACH OF CHILDREN. In case of overdose (or accidental ingestion) get medical help or contact Poison Control Center right away.
- Do not use if TAMPER EVIDENT seal is broken or missing.

INACTIVE INGREDIENTS: Ethyl Alcohol USP, Purified Water.

QUESTIONS & COMMENTS?

Natural Creations, Inc. / Woodbine, IA 51579 / 712-592-1600

REFERENCES

* The letters "HPUS" indicate that the components in this product are offically monographed in the Homeopathic Pharmacopeia of the United States.

**Claims based on traditional homeopathic practice, not accepted medical evidence. Not FDA evaluated.

PACKAGE LABEL

NDC: 43406-0695-1

STRESS / FATIGUE

HOMEOPATHIC

1 fl oz (30mL) / 20% Alcohol

877730004505